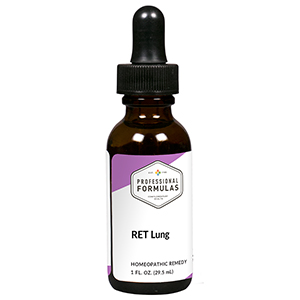 DRUG LABEL: RET Lung
NDC: 63083-7003 | Form: LIQUID
Manufacturer: Professional Complementary Health Formulas
Category: homeopathic | Type: HUMAN OTC DRUG LABEL
Date: 20190815

ACTIVE INGREDIENTS: CICHORIUM INTYBUS FLOWER 3 [hp_X]/29.5 mL; ORNITHOGALUM UMBELLATUM FLOWERING TOP 3 [hp_X]/29.5 mL; CASTANEA SATIVA FLOWER 3 [hp_X]/29.5 mL; ANHYDROUS DIBASIC CALCIUM PHOSPHATE 3 [hp_X]/29.5 mL; POTASSIUM PHOSPHATE, UNSPECIFIED FORM 3 [hp_X]/29.5 mL; GOLD 30 [hp_X]/29.5 mL; CAUSTICUM 30 [hp_X]/29.5 mL; STRYCHNOS IGNATII SEED 30 [hp_X]/29.5 mL; LACHESIS MUTA VENOM 30 [hp_X]/29.5 mL; SODIUM CHLORIDE 30 [hp_X]/29.5 mL; DELPHINIUM STAPHISAGRIA SEED 30 [hp_X]/29.5 mL
INACTIVE INGREDIENTS: ALCOHOL; WATER

RET3

ACTIVE INGREDIENTS

Chicory flower essence 3X
Star of Bethlehem flower essence 3X
Sweet chestnut flower essence 3X
Calcarea phosphorica 3X, 6X, 30X
Kali phosphoricum 3X, 6X, 30X
and all the following at 30X, 100X, 200X:
Aurum metallicum
Causticum
Ignatia amara
Lachesis mutus
Natrum muriaticum
Staphysagria

QUESTIONS

Professional Formulas

PO Box 2034 Lake Oswego, OR 97035

INDICATIONS

Temporarily relieves hopelessness, sorrow, despair, mental anguish, overprotectiveness, being easily offended, irritability, anxiousness, or dread.*

PURPOSE

*Claims based on traditional homeopathic practice, not accepted medical evidence. Not FDA evaluated.

WARNINGS

In case of overdose, get medical help or contact a poison control center right away.

Keep out of the reach of children.

PREGNANCY OR BREAST FEEDING

If pregnant or breastfeeding, ask a healthcare professional before use.

DIRECTIONS

Place drops under tongue 30 minutes before/after meals. Adults and children 12 years and over: Take 5 drops up to 4 times per day for up to one month. Consult a physician for use in children under 12 years of age.

OTHER INFORMATION

Tamper resistant. If seal is broken, do not use. After opening, close container tightly and store at room temperature away from heat.

INACTIVE INGREDIENTS

20% ethanol, purified water.

LABEL

Est 1985

Professional Formulas

Complementary Health

RET Lung

Homeopathic Remedy

1 FL. OZ. (29.5 mL)